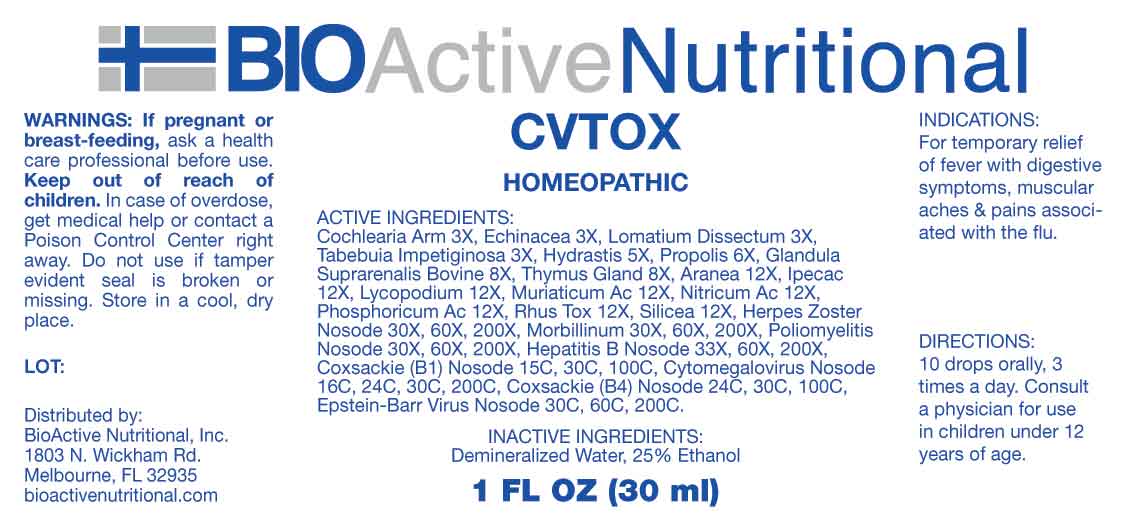 DRUG LABEL: CV TOX
NDC: 43857-0637 | Form: LIQUID
Manufacturer: BioActive Nutritional, Inc.
Category: homeopathic | Type: HUMAN OTC DRUG LABEL
Date: 20231107

ACTIVE INGREDIENTS: HORSERADISH 3 [hp_X]/1 mL; ECHINACEA ANGUSTIFOLIA WHOLE 3 [hp_X]/1 mL; LOMATIUM DISSECTUM ROOT 3 [hp_X]/1 mL; HANDROANTHUS IMPETIGINOSUS BARK 3 [hp_X]/1 mL; GOLDENSEAL 5 [hp_X]/1 mL; PROPOLIS WAX 6 [hp_X]/1 mL; BOS TAURUS ADRENAL GLAND 8 [hp_X]/1 mL; SUS SCROFA THYMUS 8 [hp_X]/1 mL; ARANEUS DIADEMATUS 12 [hp_X]/1 mL; IPECAC 12 [hp_X]/1 mL; LYCOPODIUM CLAVATUM SPORE 12 [hp_X]/1 mL; HYDROCHLORIC ACID 12 [hp_X]/1 mL; NITRIC ACID 12 [hp_X]/1 mL; PHOSPHORIC ACID 12 [hp_X]/1 mL; TOXICODENDRON PUBESCENS LEAF 12 [hp_X]/1 mL; SILICON DIOXIDE 12 [hp_X]/1 mL; HUMAN HERPESVIRUS 3 30 [hp_X]/1 mL; MEASLES VIRUS 30 [hp_X]/1 mL; POLIOVIRUS 30 [hp_X]/1 mL; HEPATITIS B VIRUS 33 [hp_X]/1 mL; HUMAN COXSACKIEVIRUS B1 15 [hp_C]/1 mL; HUMAN HERPESVIRUS 5 16 [hp_C]/1 mL; HUMAN COXSACKIEVIRUS B4 24 [hp_C]/1 mL; HUMAN HERPESVIRUS 4 30 [hp_C]/1 mL
INACTIVE INGREDIENTS: WATER; ALCOHOL

DRUG FACTS:

ACTIVE INGREDIENTS:

Cochlearia Armoracia 3X, Echinacea 3X, Lomatium Dissectum 3X, Tabebuia Impetiginosa 3X, Hydrastis Canadensis 5X, Propolis 6X, Glandula Suprarenalis Bovine 8X, Thymus Gland 8X, Aranea Diadema 12X, Ipecacuanha 12X, Lycopodium Clavatum 12X, Muriaticum Acidum 12X, Nitricum Acidum 12X, Phosphoricum Acidum 12X, Rhus Tox 12X, Silicea 12X, Herpes Zoster Nosode 30X, 60X, 200X, Morbillinum 30X, 60X, 200X, Poliomyelitis Nosode 30X, 60X, 200X, Hepatitis B Nosode 33X, 60X, 200X, Coxsackie B1 Nosode 15C, 30C, 100C, Cytomegalovirus Nosode 16C, 24C, 30C, 200C, Coxsackie B4 Nosode 24C, 30C, 100C, Epstein-Barr Virus Nosode 30C, 60C, 200C.

PURPOSE:

For temporary relief of fever with digestive symptoms, muscular aches & pains associated with the flu.

WARNINGS:

If pregnant or breast-feeding, ask a health care professional before use.

Keep out of reach of children. In case of overdose, get medical help or contact a Poison Control Center right away.

Do not use if tamper evident seal is broken or missing.

Store in cool, dry place.

KEEP OUT OF REACH OF CHILDREN:

In case of overdose, get medical help or contact a Poison Control Center right away.

DIRECTIONS:

10 drops orally, 3 times a day. Consult a physician for use in children under 12 years of age.

INDICATIONS:

For temporary relief of fever with digestive symptoms, muscular aches & pains associated with the flu.

INACTIVE INGREDIENTS:

Demineralized Water, 25% Ethanol

QUESTIONS:

Distributed by:

BioActive Nutritional, Inc.

1803 N. Wickham Rd.

Melbourne, FL 32935

bioactivenutritional.com

PACKAGE LABEL DISPLAY:

BIOActive Nutritional

CVTOX

HOMEOPATHIC

1 FL OZ (30 ml)